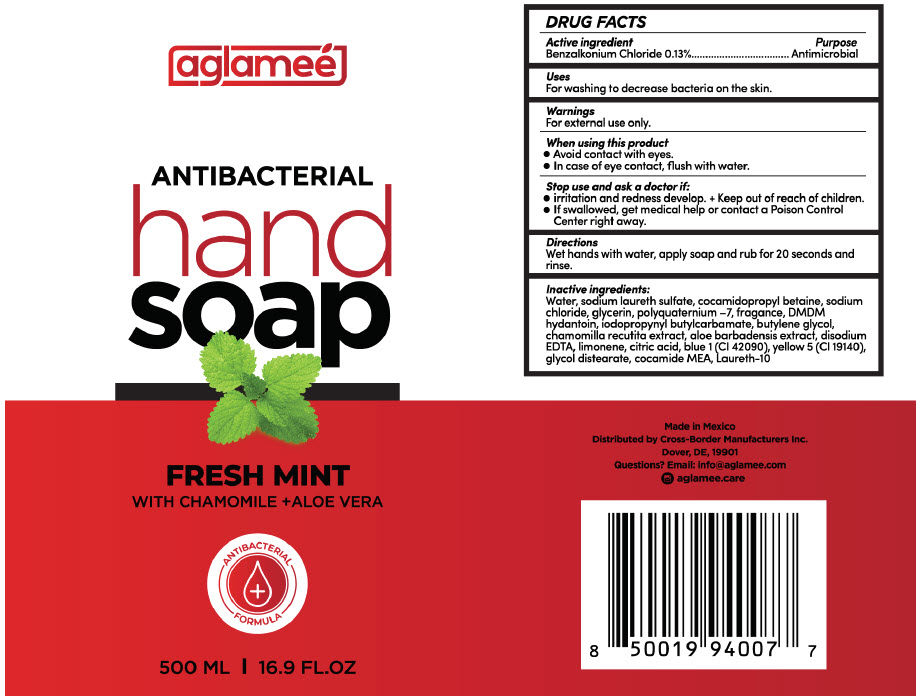 DRUG LABEL: ANTIBACTERIAL Hand
NDC: 78939-002 | Form: LIQUID
Manufacturer: CROSS BORDER MANUFACTURERS INC.
Category: otc | Type: HUMAN OTC DRUG LABEL
Date: 20200922

ACTIVE INGREDIENTS: BENZALKONIUM CHLORIDE 1.3 mg/1 mL
INACTIVE INGREDIENTS: WATER; SODIUM LAURETH-3 SULFATE; COCAMIDOPROPYL BETAINE; SODIUM CHLORIDE; GLYCERIN; POLYQUATERNIUM-7 (70/30 ACRYLAMIDE/DADMAC; 1600000 MW); DMDM HYDANTOIN; IODOPROPYNYL BUTYLCARBAMATE; BUTYLENE GLYCOL; EDETATE DISODIUM ANHYDROUS; LIMONENE, (+)-; CITRIC ACID MONOHYDRATE; FD&C BLUE NO. 1; FD&C YELLOW NO. 5; GLYCOL DISTEARATE; COCO MONOETHANOLAMIDE; LAURETH-10

ANTIBACTERIAL Hand Soap

DRUG FACTS

Active ingredient

Benzalkonium Chloride 0.13%

Purpose

Antimicrobial

Uses

For washing to decrease bacteria on the skin.

Warnings

For external use only.

When using this product

- Avoid contact with eyes.
- In case of eye contact, flush with water.

Stop use and ask a doctor if

- irritation and redness develop.

+ Keep out of reach of children.

- If swallowed, get medical help or contact a Poison Control Center right away.

Directions

Wet hands with water, apply soap and rub for 20 seconds and rinse.

Inactive ingredients

Water, sodium laureth sulfate, cocamidopropyl betaine, sodium chloride, glycerin, polyquaternium –7, fragance, DMDM hydantoin, iodopropynyl butylcarbamate, butylene glycol, chamomilla recutita extract, aloe barbadensis extract, disodium EDTA, limonene, citric acid, blue 1 (CI 42090), yellow 5 (CI 19140), glycol distearate, cocamide MEA, Laureth-10

Questions?

Email: info@aglamee.com

Distributed by Cross-Border Manufacturers Inc.
Dover, DE, 19901

PRINCIPAL DISPLAY PANEL - 500 ML Bottle Label

aglameé

ANTIBACTERIAL
hand
soap

FRESH MINT
WITH CHAMOMILE +ALOE VERA

ANTIBACTERIAL
FORMULA

500 ML | 16.9 FL.OZ